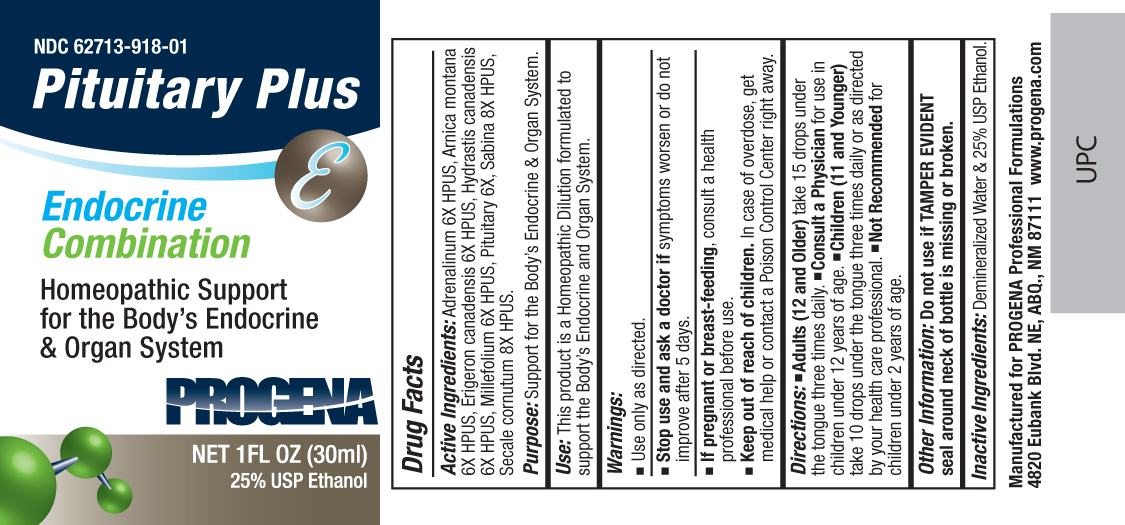 DRUG LABEL: Progena
NDC: 62713-918 | Form: LIQUID
Manufacturer: Meditrend, Inc. DBA Progena Professional Formulations
Category: homeopathic | Type: HUMAN OTC DRUG LABEL
Date: 20151207

ACTIVE INGREDIENTS: EPINEPHRINE 6 [hp_X]/1 mL; ARNICA MONTANA 6 [hp_X]/1 mL; CONYZA CANADENSIS 6 [hp_X]/1 mL; GOLDENSEAL 6 [hp_X]/1 mL; ACHILLEA MILLEFOLIUM 6 [hp_X]/1 mL; SUS SCROFA PITUITARY GLAND 6 [hp_X]/1 mL; JUNIPERUS SABINA LEAFY TWIG 8 [hp_X]/1 mL; CLAVICEPS PURPUREA SCLEROTIUM 8 [hp_X]/1 mL
INACTIVE INGREDIENTS: WATER; ALCOHOL

Pituitary Plus

ACTIVE INGREDIENT

Active Ingredients:Adrenalinum 6X HPUS, Arnica montana 6X HPUS, Erigeron canadensis 6X HPUS, Hydrastis canadensis 6X HPUS, Millefolium 6X HPUS, Pituitary 6X, Sabina 8X HPUS, Secale cornutum 8X HPUS.

PURPOSE

Purpose:Support for the Body's Endocrine and Organ System.

INDICATIONS AND USAGE

Use:This product is a Homeopathic Dilution formulated to support the Body's Endocrine and Organ System.

Keep Out of Reach of Children. In case of overdose, get medical help or contact a
Poison Control Center right away.

Warnings:

- Use Only as directed.
- Stop use and ask a doctor ifsymptoms worsen or do not improve after 5 days.
- If pregnant or breast-feeding, consult a health professional before use.

DOSAGE AND ADMINISTRATION

Directions:• Adults (12 and Older)take 15 drops under the tongue three times daily.• Consult a Physicianfor use in children under 12 years of age.• Children (11 and Younger)take 10 drops under the tongue three times daily or as directed by your health care professional.• Not Recommendedfor children under 2 years of age.

Other Information: Do not use if TAMPER EVIDENT seal around neck of bottle is missing or broken.

INACTIVE INGREDIENT

Inactive Ingredients:USP Purified Water and 25% USP Ethanol.

PACKAGE LABEL

Manufactured for Progena Professional Formulations
4820 Eubank Blvd. NE, ABQ, NM 87111, www.progena.com